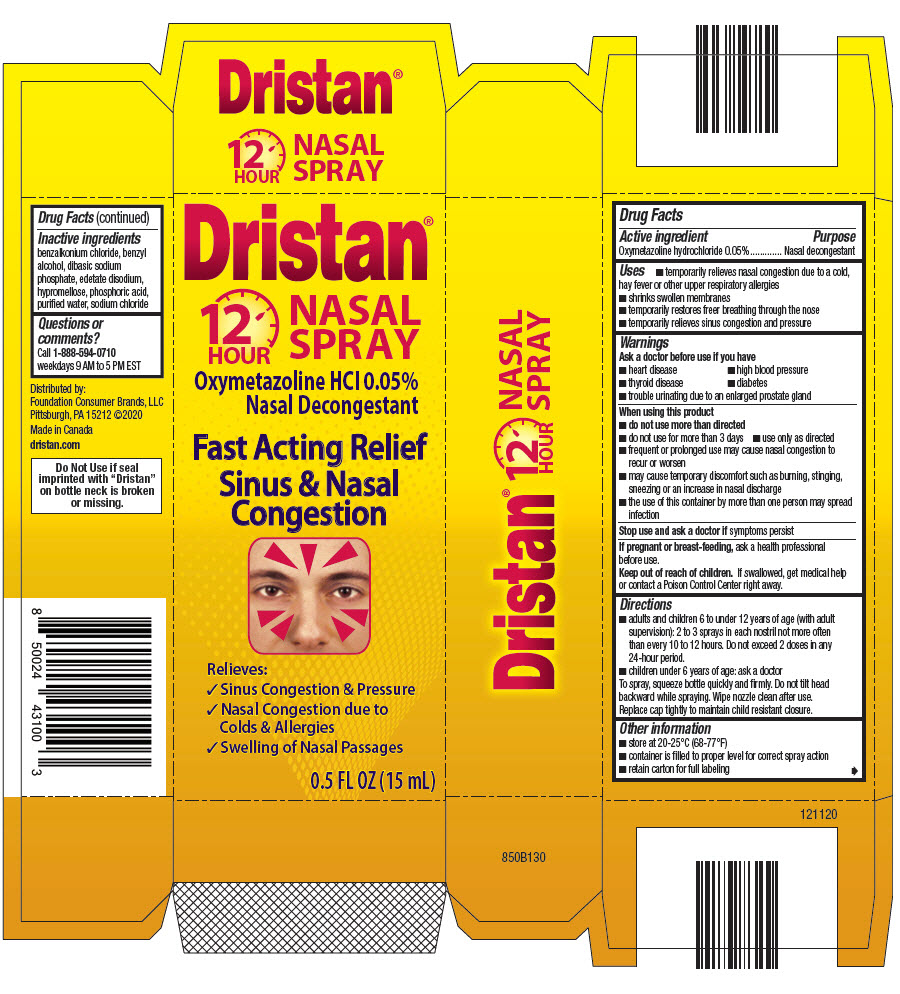 DRUG LABEL: Dristan
NDC: 80070-400 | Form: SPRAY
Manufacturer: Foundation Consumer Brands
Category: otc | Type: HUMAN OTC DRUG LABEL
Date: 20251024

ACTIVE INGREDIENTS: OXYMETAZOLINE HYDROCHLORIDE 0.5 mg/1 mL
INACTIVE INGREDIENTS: BENZALKONIUM CHLORIDE; BENZYL ALCOHOL; SODIUM PHOSPHATE, DIBASIC, UNSPECIFIED FORM; HYPROMELLOSE, UNSPECIFIED; PHOSPHORIC ACID; WATER; SODIUM CHLORIDE; EDETATE DISODIUM

Dristan®
12 hr

Drug Facts

Active ingredient

Oxymetazoline hydrochloride 0.05%

Purpose

Nasal decongestant

Uses

- temporarily relieves nasal congestion due to a cold, hay fever or other upper respiratory allergies
- shrinks swollen membranes
- temporarily restores freer breathing through the nose
- temporarily relieves sinus congestion and pressure

Warnings

Ask a doctor before use if you have

- heart disease
- high blood pressure
- thyroid disease
- diabetes
- trouble urinating due to an enlarged prostate gland

When using this product

- do not use more than directed
- do not use for more than 3 days
- use only as directed
- frequent or prolonged use may cause nasal congestion to recur or worsen
- may cause temporary discomfort such as burning, stinging, sneezing or an increase in nasal discharge
- the use of this container by more than one person may spread infection

Stop use and ask a doctor ifsymptoms persist

PREGNANCY OR BREAST FEEDING

If pregnant or breast-feeding,ask a health professional before use.

Keep out of reach of children.If swallowed, get medical help or contact a Poison Control Center right away.

Directions

- adults and children 6 to under 12 years of age (with adult supervision): 2 to 3 sprays in each nostril not more often than every 10 to 12 hours. Do not exceed 2 doses in any 24-hour period.
- children under 6 years of age: ask a doctor To spray, squeeze bottle quickly and firmly. Do not tilt head backward while spraying. Wipe nozzle clean after use. Replace cap tightly to maintain child resistant closure.

Other information

- store at 20-25°C (68-77°F)
- container is filled to proper level for correct spray action
- retain carton for full labeling

Inactive ingredients

benzalkonium chloride, benzyl alcohol, dibasic sodium phosphate, edetate disodium, hypromellose, phosphoric acid, purified water, sodium chloride

Questions or comments?

Call 1-888-594-0710weekdays 9 AM to 5 PM EST

Distributed by:
Foundation Consumer Brands, LLC
Pittsburgh, PA 15212

PRINCIPAL DISPLAY PANEL - 15 mL Bottle Carton

Dristan®
12
HOUR
NASAL
SPRAY

Oxymetazoline HCl 0.05%
Nasal Decongestant

Fast Acting Relief
Sinus & Nasal
Congestion

Relieves:

- Sinus Congestion & Pressure
- Nasal Congestion due to
  Colds & Allergies
- Swelling of Nasal Passages

0.5 FL OZ (15 mL)